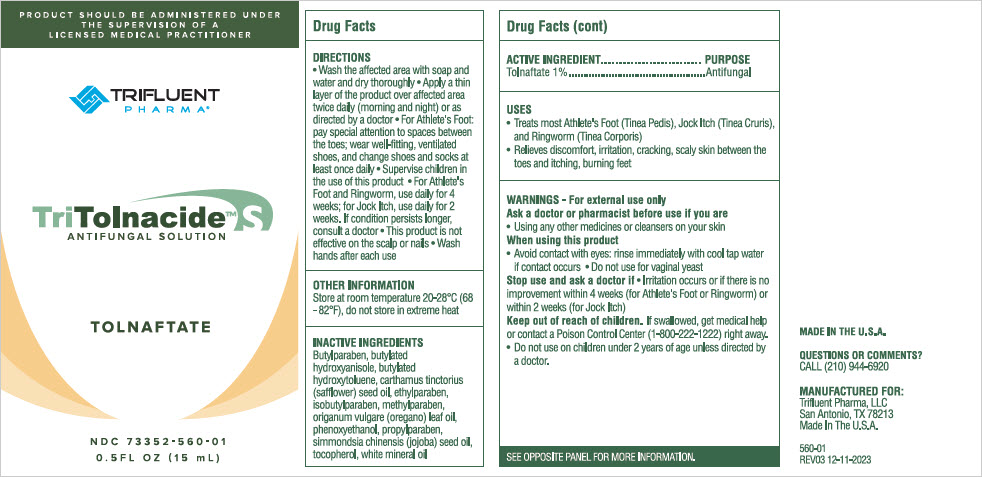 DRUG LABEL: Tritolnacide S
NDC: 73352-560 | Form: SOLUTION
Manufacturer: Trifluent Pharma LLC
Category: otc | Type: HUMAN OTC DRUG LABEL
Date: 20251014

ACTIVE INGREDIENTS: TOLNAFTATE 0.01 g/1 mL
INACTIVE INGREDIENTS: MINERAL OIL; SAFFLOWER OIL; JOJOBA OIL; BUTYLATED HYDROXYTOLUENE; BUTYLATED HYDROXYANISOLE; OREGANO LEAF OIL; .ALPHA.-TOCOPHEROL; PHENOXYETHANOL; METHYLPARABEN; ETHYLPARABEN; ISOBUTYLPARABEN; BUTYLPARABEN; PROPYLPARABEN

TriTolnacide™ S

DRUG FACTS

ACTIVE INGREDIENT

Tolnaftate 1%

PURPOSE

Antifungal

USES

- Treats most Athlete's Foot (Tinea Pedis), Jock Itch (Tinea Cruris), and Ringworm (Tinea Corporis)
- Relieves discomfort, irritation, cracking, scaly skin between the toes and itching, burning feet.

WARNINGS

For external use only.

Ask a doctor or pharmacist before use if you are

- Using any other medicines or cleansers on your skin

When using this product

- Avoid contact with eyes: rinse immediately with cool tap water if contact occurs.
- Do not use for vaginal yeast

Stop use and ask a doctor if

- Irritation occurs or if there is no improvement within 4 weeks (for Athlete's Foot or Ringworm) or within 2 weeks (for Jock Itch)

Keep out of reach of children. If swallowed, get medical help or contact a Poison Control Center (1-800-222-1222) right away.

- Do not use on children under 2 years of age unless directed by a doctor.

DIRECTIONS

- Wash the affected area with soap and water and dry thoroughly
- Apply a thin layer of the product over the affected area twice daily (morning and night), or as directed by a doctor
- For Athlete's Foot: pay special attention to spaces between the toes; wear well-fitting, ventilated shoes and change shoes and socks at least once daily
- Supervise children in the use of this product
- For Athlete's Foot and Ringworm, use daily for 4 weeks; for Jock Itch, use daily for 2 weeks. If condition persists longer, consult a doctor
- This product is not effective on the scalp or nails
- Wash hands after each use

INACTIVE INGREDIENTS

Butylparaben, butylated hydroxyanisole, butylated hydroxytoluene, Carthamus tinctorius (safflower) seed oil, ethylparaben, isobutylparaben, methylparaben, Origanum vulgare (oregano) leaf oil, phenoxyethanol, propylparaben, Simmondsia chinensis (jojoba) seed oil, tocopherol, white mineral oil.

QUESTIONS OR COMMENTS?

CALL (210) 944-6920

PRINCIPAL DISPLAY PANEL - 15 mL Bottle Label

PRODUCT SHOULD BE ADMINISTERED UNDER
THE SUPERVISION OF A
LICENSED MEDICAL PRACTITIONER

TRIFLUENT
PHARMA®

TriTolnacide™ S
ANTIFUNGAL SOLUTION

TOLNAFTATE

NDC 73352-560-01
0.5FL OZ (15 mL)